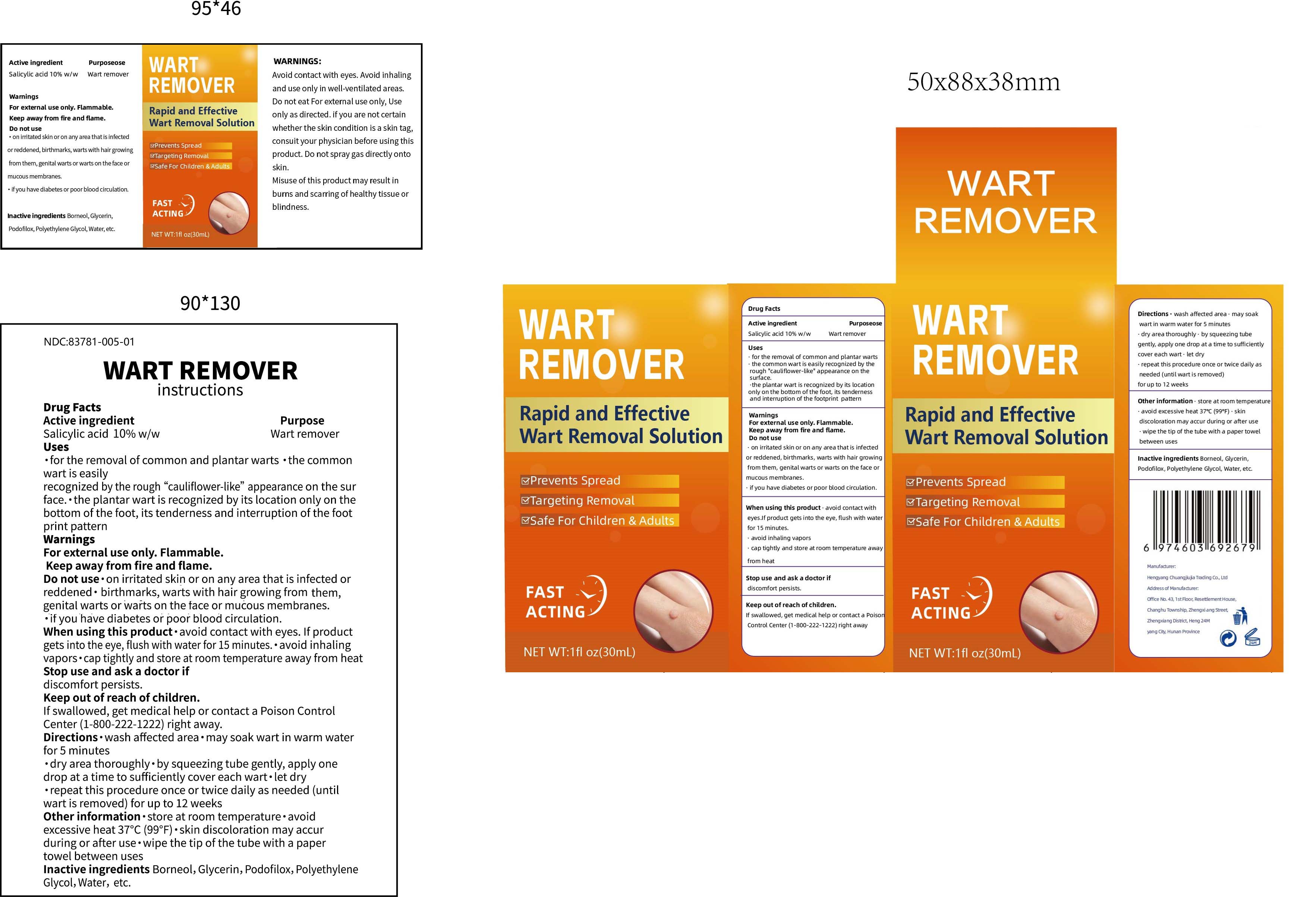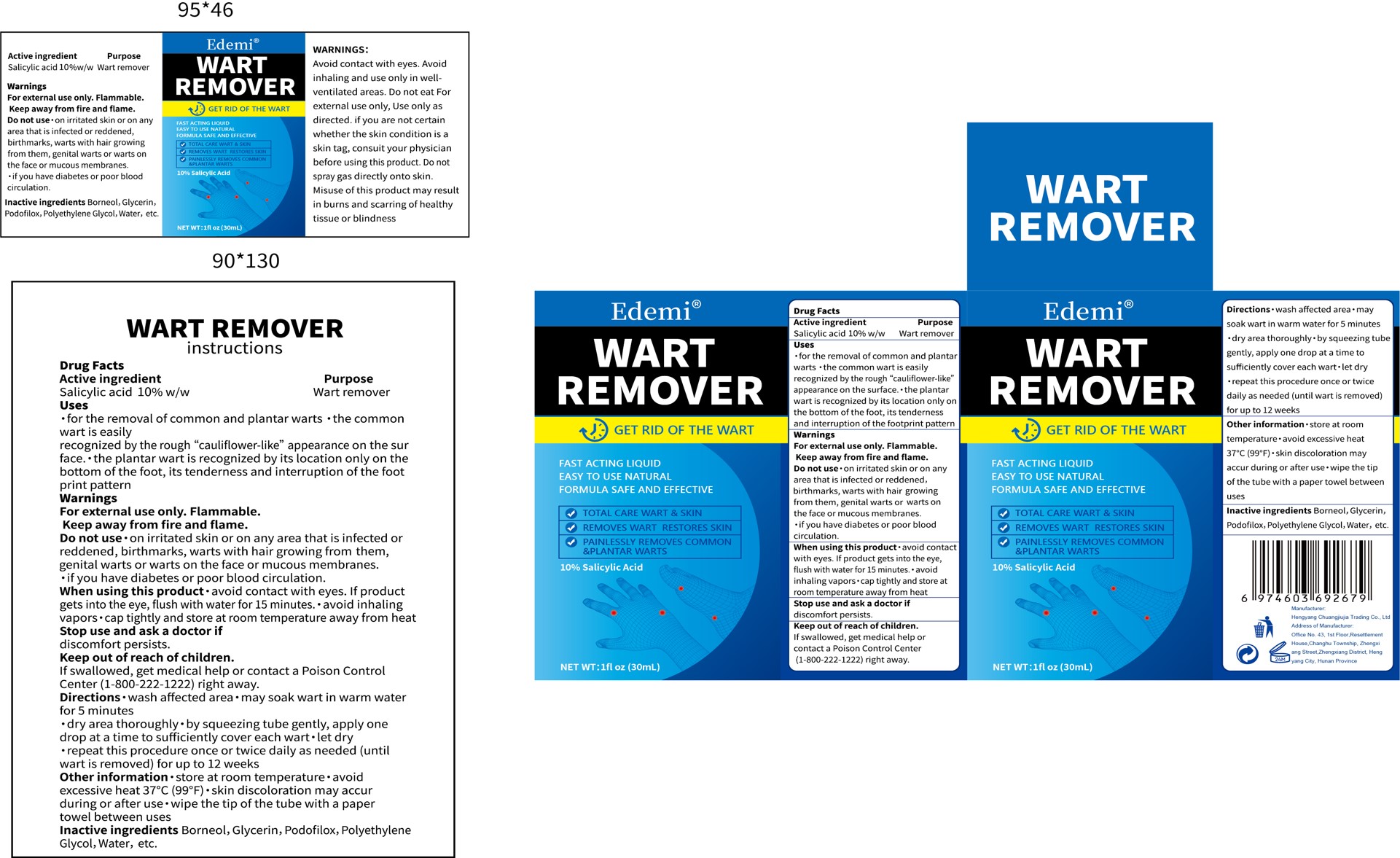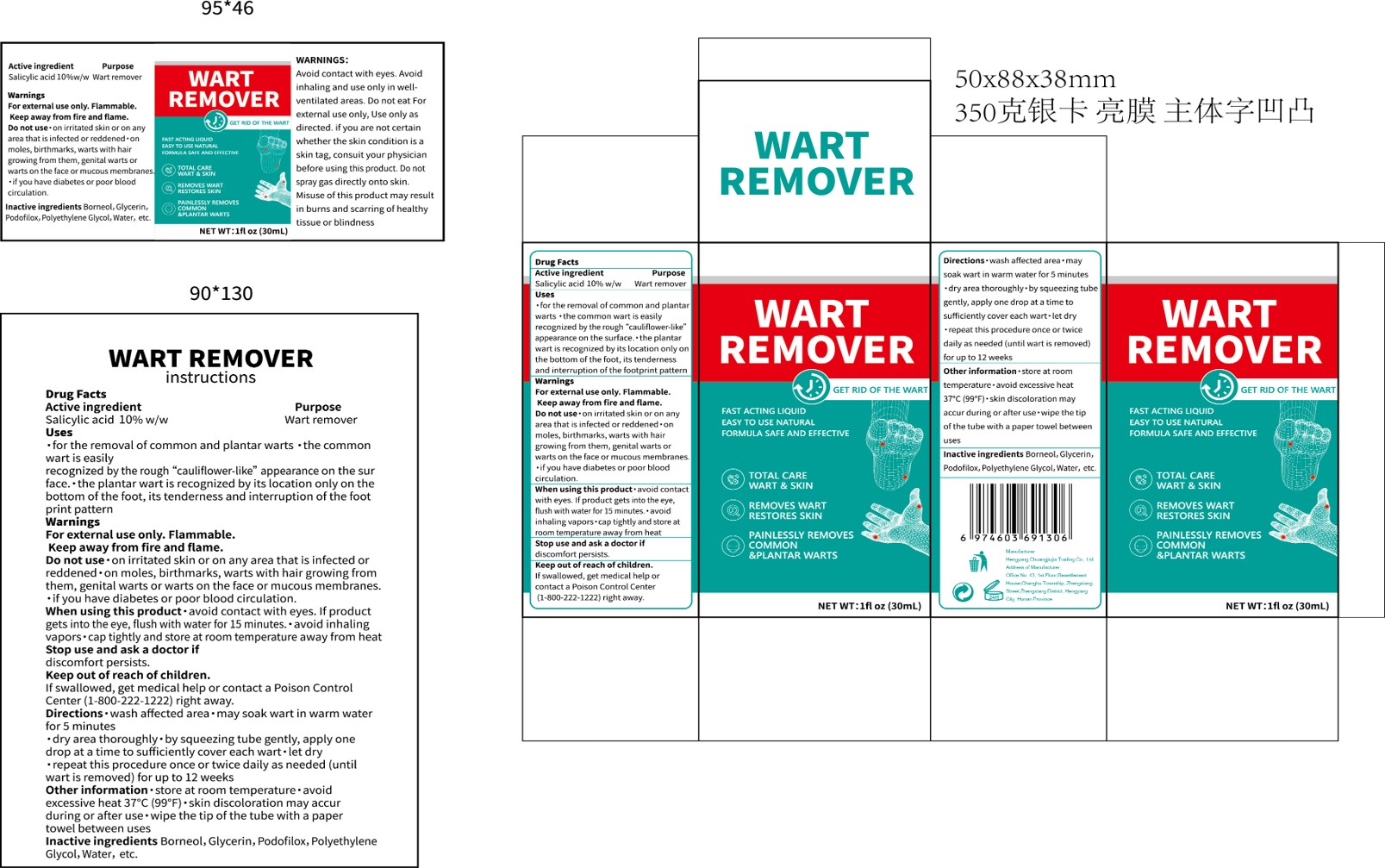 DRUG LABEL: Wart remover
NDC: 84735-002 | Form: LIQUID
Manufacturer: Hengyang Chuangjiujia Trading Co., Ltd.
Category: otc | Type: HUMAN OTC DRUG LABEL
Date: 20241229

ACTIVE INGREDIENTS: SALICYLIC ACID 0.1 g/1 mL
INACTIVE INGREDIENTS: WATER; PODOFILOX; POLYETHYLENE; BORNEOL; GLYCERIN; GLYCOL

Wart remover

Wart remover

ACTIVE INGREDIENT

Salicylic acid 10%

PURPOSE

Wart remover

INDICATIONS AND USAGE

for the removal of common and plantar warts ·the commonwart is easilyrecognized by the rough “cauliflower-like” appearance on the surface. the plantar wart is recognized by its location only on thebottom of the foot, its tenderness and interruption of the footprint pattern

WARNINGS

For externaluse only.Flammable.

Do not use on irritated skin or on any area that is infected orreddened·birthmarks, warts with hair growing from them,genital warts or warts on the face or mucous membranes
if you have diabetes or poor blood circulation.

When using this product·avoid contact with eyes. lf productgets into the eye, flush with water for 15 minutes. avoid inhalingvapors. cap tightly and store at room temperature away from heat

Stop use and ask a doctor if
discomfort persists.

KEEP OUT OF REACH OF CHILDREN

If swallowed, get medical help or contact a Poison Control Center(1-800-222-1222)right away.

DOSAGE AND ADMINISTRATION

Directions·wash affected area may soak wart in warm waterfor 5 minutes·

dry area thoroughly·by squeezing tube gently, apply onedrop at a time to sufficiently cover each wart·let dry.

repeat this procedure once or twice daily as needed (untiwart is removed) for up to 12 weeks

Other information·store at room temperature avoidexcessive heat 37°℃ (99°F)·skin discoloration may accurduring or after use wipe the tip of the tube with a papertowel between uses

INACTIVE INGREDIENT

Borneol
Glycerin
Podofilox
Polyethylene
Glycol
Water